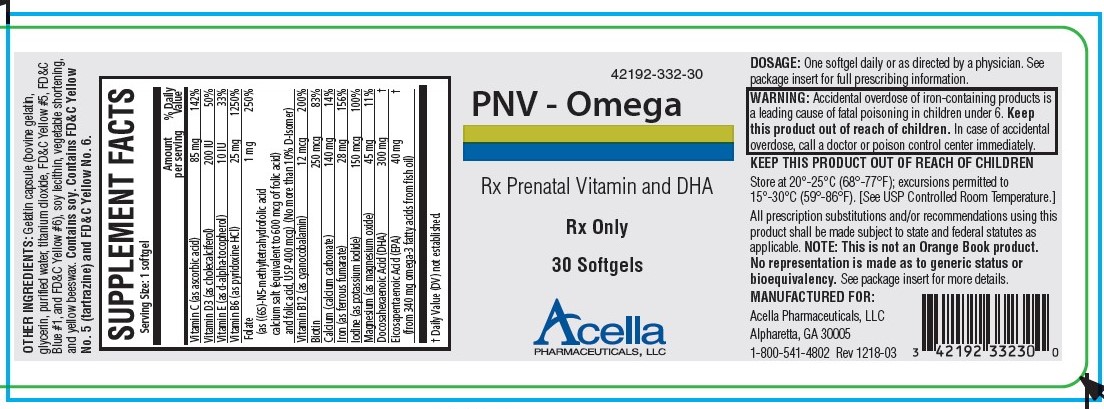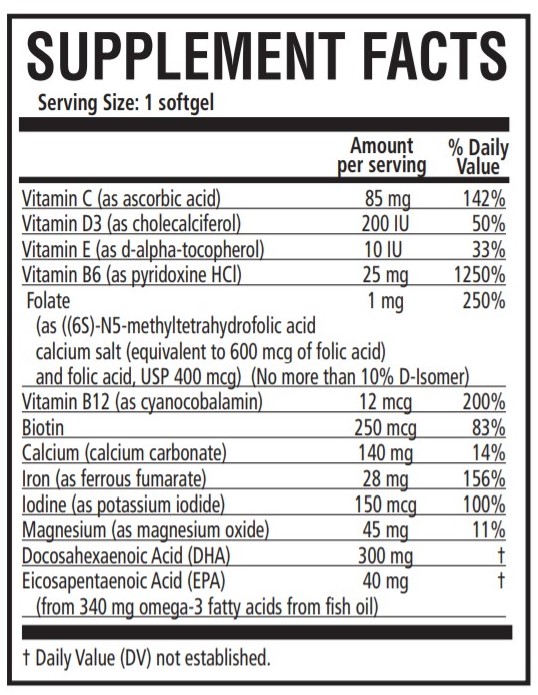 DRUG LABEL: PNV-Omega
NDC: 42192-332 | Form: CAPSULE, GELATIN COATED
Manufacturer: Acella Pharmaceuticals, LLC
Category: prescription | Type: HUMAN PRESCRIPTION DRUG LABEL
Date: 20240115

ACTIVE INGREDIENTS: ASCORBIC ACID 85 mg/1 1; CHOLECALCIFEROL 200 [iU]/1 1; .ALPHA.-TOCOPHEROL 10 [iU]/1 1; PYRIDOXINE 25 mg/1 1; FOLIC ACID 1 mg/1 1; CYANOCOBALAMIN 12 ug/1 1; BIOTIN 250 ug/1 1; CALCIUM CARBONATE 140 mg/1 1; FERROUS FUMARATE 28 mg/1 1; POTASSIUM IODIDE 150 ug/1 1; MAGNESIUM OXIDE 45 mg/1 1; DOCONEXENT 300 mg/1 1; ICOSAPENT 40 mg/1 1
INACTIVE INGREDIENTS: YELLOW WAX; CORN OIL; LECITHIN, SOYBEAN; GELATIN; GLYCERIN; WATER; TITANIUM DIOXIDE; FD&C BLUE NO. 1; FD&C RED NO. 3

PNV - Omega

PNV - Omega

Rx Only

DESCRIPTION

PNV-Omega is a prescription prenatal/postnatal dietary supplement softgel capsule that contains multivitamins and minerals along with essential fatty acids. Each softgel is green in color, opaque and imprinted with “332” on one side.

OTHER INGREDIENTS

Gelatin capsule (bovine gelatin, glycerin, purified water, titanium dioxide, FD&C Yellow #5, FD&C Blue #1, and FD&C Yellow #6), soy lecithin, vegetable shortening, and yellow beeswax. Contains soy. Contains FD&C Yellow No. 5 (tartrazine) and FD&C Yellow No. 6.

INDICATIONS

PNV - Omega is a multivitamin/ multimineral dietary supplement indicated for use in the dietary management of patients with nutritional deficiencies or are in need of nutritional supplementation.

CONTRAINDICATIONS

This product is contraindicated in patients with a known hypersensitivity to any of the ingredients.

WARNING

Ingestion of more than 3 grams of omega-3 fatty acids (such as DHA) per day has been shown to have potential antithrombotic effects, including an increased bleeding time and International Normalized Ratio (INR). Administration of omega-3 fatty acids should be avoided in patients taking anticoagulants and in those known to have an inherited or acquired predisposition to bleeding.

WARNING

Accidental overdose of iron-containing products is a leading cause of fatal poisoning in children under 6. Keep this product out of reach of children. In case of accidental overdose, call a doctor or poison control center immediately.

PRECAUTIONS

Folic acid alone is improper therapy in the treatment of pernicious anemia and other megaloblastic anemias where Vitamin B12 is deficient. Folic acid in doses above 1.0 mg daily may obscure pernicious anemia in that hematologic remission can occur while neurological manifestations progress.

ADVERSE REACTIONS

Allergic sensitization has been reported following both oral and parenteral administration of folic acid.

DOSAGE AND ADMINISTRATION

Before, during and/or after pregnancy, one softgel daily or as directed by a physician.

HOW SUPPLIED

PNV - Omega is supplied in child-resistant bottles of 30 softgels (42192-332-30). The listed product is not a National Drug Code, but has merely been formatted to comply with standard industry practice for pharmacy and insurance computer systems.

Store at 20°-25°C (68°-77°F); excursions permitted to 15°-30°C (59°-86°F). [See USP Controlled Room Temperature.]

KEEP THIS AND ALL MEDICATIONS OUT OF THE REACH OF CHILDREN.

KEEP THIS AND ALL MEDICATIONS OUT OF THE REACH OF CHILDREN.

All prescription substitutions and/or recommendations using this product shall be made subject to state and federal statutes as applicable. Please note: this is not an Orange Book product and has not been subjected to FDA therapeutic equivalency or other equivalency testing. No representation is made as to generic status or bioequivalency. Each person recommending a prescription substitution using this product shall make such recommendations based on each such person’s professional opinion and knowledge, upon evaluating the dietary ingredients, other ingredients and information provided herein.
THESE STATEMENTS HAVE NOT BEEN EVALUATED BY THE FOOD AND DRUG ADMINISTRATION. THIS PRODUCT IS NOT INTENDED TO DIAGNOSE, TREAT, CURE OR PREVENT ANY DISEASE.

MANUFACTURED FOR:

Acella Pharmaceuticals, LLC

Alpharetta, GA 30005

1-800-541-4802

Rev 1218-04

PRINCIPAL DISPLAY PANEL - 30 Softgel Tablets

NDC 42192-332-30

PNV - Omega

Rx Prenatal Vitamin and DHA

Rx Only

30 Softgels

Acella PHARMACEUTICALS, LLC